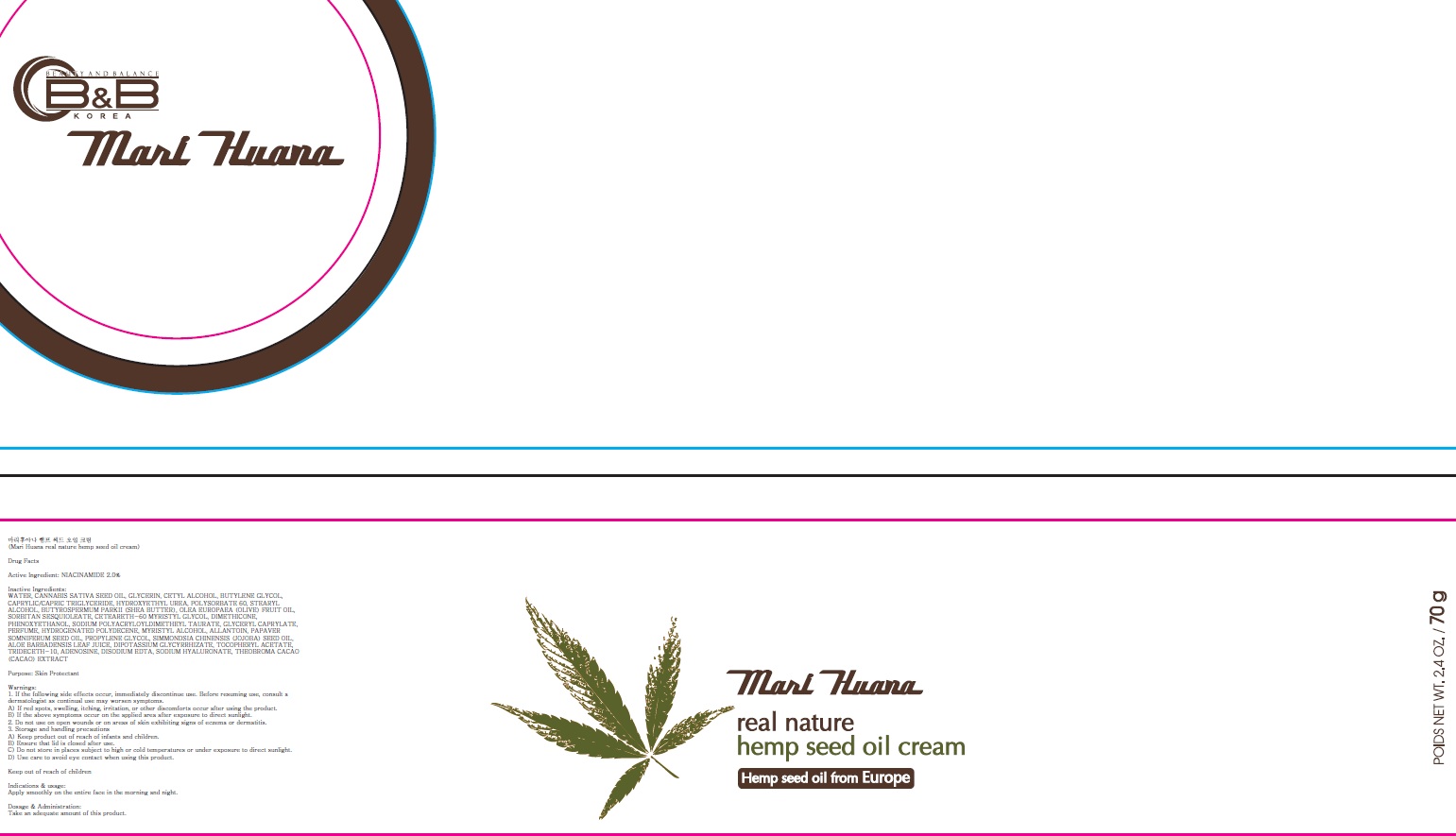 DRUG LABEL: Mari Huana real nature hemp seed
NDC: 70603-030 | Form: CREAM
Manufacturer: JUNGLEFOOD CO., LTD.
Category: otc | Type: HUMAN OTC DRUG LABEL
Date: 20160408

ACTIVE INGREDIENTS: NIACINAMIDE 1.4 g/70 g
INACTIVE INGREDIENTS: WATER; CANNABIS SATIVA SEED OIL

ACTIVE INGREDIENT

Active Ingredient: NIACINAMIDE 2.0%

INACTIVE INGREDIENT

Inactive Ingredients: WATER, CANNABIS SATIVA SEED OIL, GLYCERIN, CETYL ALCOHOL, BUTYLENE GLYCOL, CAPRYLIC/CAPRIC TRIGLYCERIDE, HYDROXYETHYL UREA, POLYSORBATE 60, STEARYL ALCOHOL, BUTYROSPERMUM PARKII (SHEA BUTTER), OLEA EUROPAEA (OLIVE) FRUIT OIL, SORBITAN SESQUIOLEATE, CETEARETH-60 MYRISTYL GLYCOL, DIMETHICONE, PHENOXYETHANOL, SODIUM POLYACRYLOYLDIMETHEYL TAURATE, GLYCERYL CAPRYLATE, PERFUME, HYDROGENATED POLYDECENE, MYRISTYL ALCOHOL, ALLANTOIN, PAPAVER SOMNIFERUM SEED OIL, PROPYLENE GLYCOL, SIMMONDSIA CHINENSIS (JOJOBA) SEED OIL, ALOE BARBADENSIS LEAF JUICE, DIPOTASSIUM GLYCYRRHIZATE, TOCOPHERYL ACETATE, TRIDECETH-10, ADENOSINE, DISODIUM EDTA, SODIUM HYALURONATE, THEOBROMA CACAO (CACAO) EXTRACT

PURPOSE

Purpose: Skin Protectant

WARNINGS

Warnings: 1. If the following side effects occur, immediately discontinue use. Before resuming use, consult a dermatologist as continual use may worsen symptoms. A) If red spots, swelling, itching, irritation, or other discomforts occur after using the product. B) If the above symptoms occur on the applied area after exposure to direct sunlight. 2. Do not use on open wounds or on areas of skin exhibiting signs of eczema or dermatitis. 3. Storage and handling precautions A) Keep product out of reach of infants and children. B) Ensure that lid is closed after use. C) Do not store in places subject to high or cold temperatures or under exposure to direct sunlight. D) Use care to avoid eye contact when using this product.

KEEP OUT OF REACH OF CHILDREN

INDICATIONS & USAGE

Indications & usage: Apply smoothly on the entire face in the morning and night.

DOSAGE & ADMINISTRATION

Dosage & Administration: Take an adequate amount of this product.